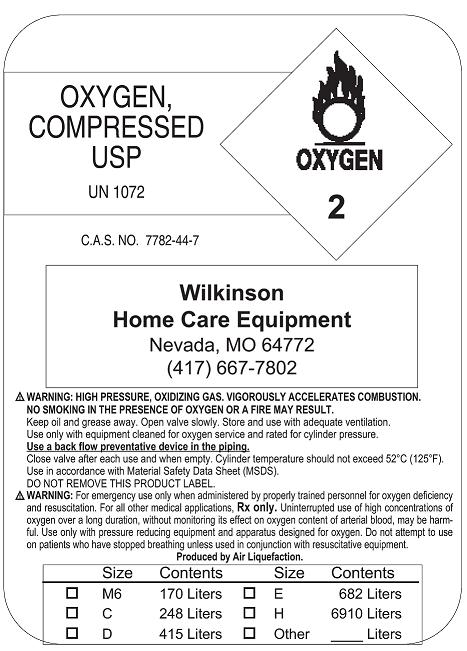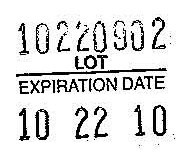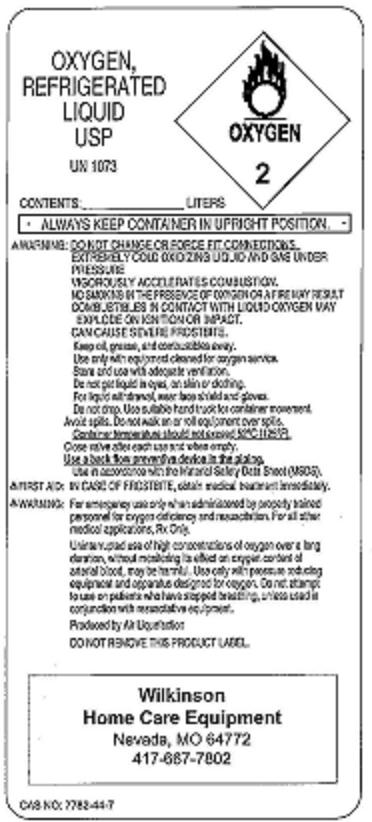 DRUG LABEL: Oxygen
NDC: 24846-0001 | Form: GAS
Manufacturer: Wilkinson Pharmacy, Inc.
Category: prescription | Type: HUMAN PRESCRIPTION DRUG LABEL
Date: 20091029

ACTIVE INGREDIENTS: Oxygen 99 L/100 L

Oxygen